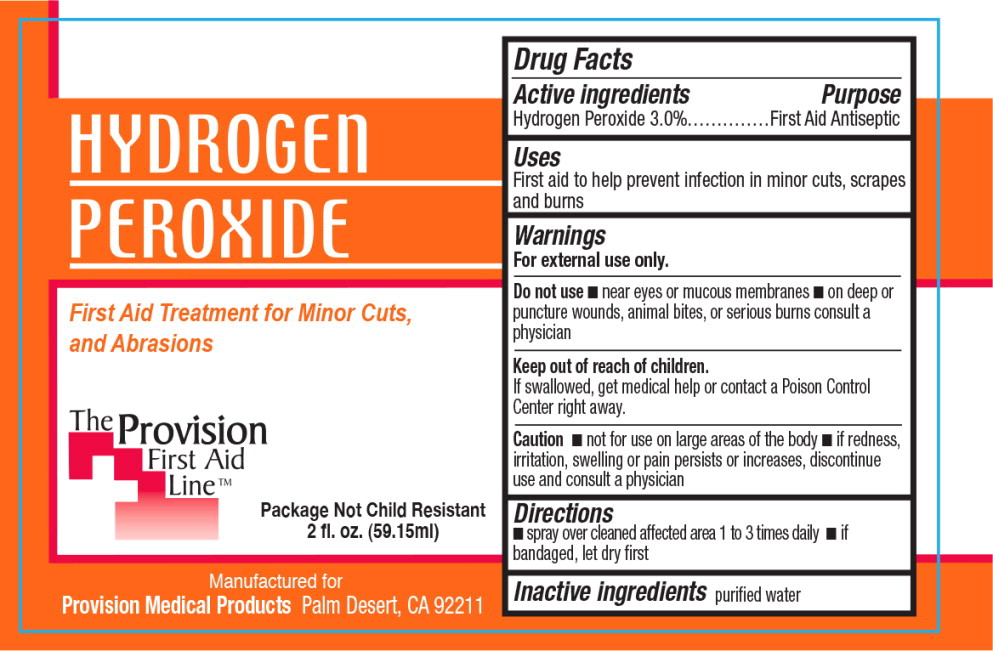 DRUG LABEL: Hydrogen Peroxide
NDC: 69103-3503 | Form: SPRAY
Manufacturer: Provision Medical
Category: otc | Type: HUMAN OTC DRUG LABEL
Date: 20140829

ACTIVE INGREDIENTS: hydrogen peroxide 30 mL/1 L
INACTIVE INGREDIENTS: water

Drug Facts

Active ingredients

Hydrogen Peroxide 3.0%

Purpose

First Aid Antiseptic

Uses

First aid to help prevent infection in minor cuts, scrapes and burns

Warnings

For external use only.

Do not use

- near eyes or mucous membranes
- on deep or puncture wounds, animal bites, or serious burns consult a physician

Keep out of reach of children.

If swallowed, get medical help or contact a Poison Control Center right away.

Caution

- not for use on large areas of the body
- if redness, irritation, swelling or pain persists or increases, discontinue use and consult a physician

Directions

- spray over cleaned affected area 1 to 3 times daily
- if bandaged, let dry first

Inactive ingredients

purified water

Principal Display Panel - Bottle Label

HYDROGEN
PEROXIDE

First Aid Treatment for Minor Cuts,
and Abrasions

Package Not Child Resistant

2 fl. oz. (59.15ml)

Manufactured for

Provision Medical Products Palm Desert, CA 92211